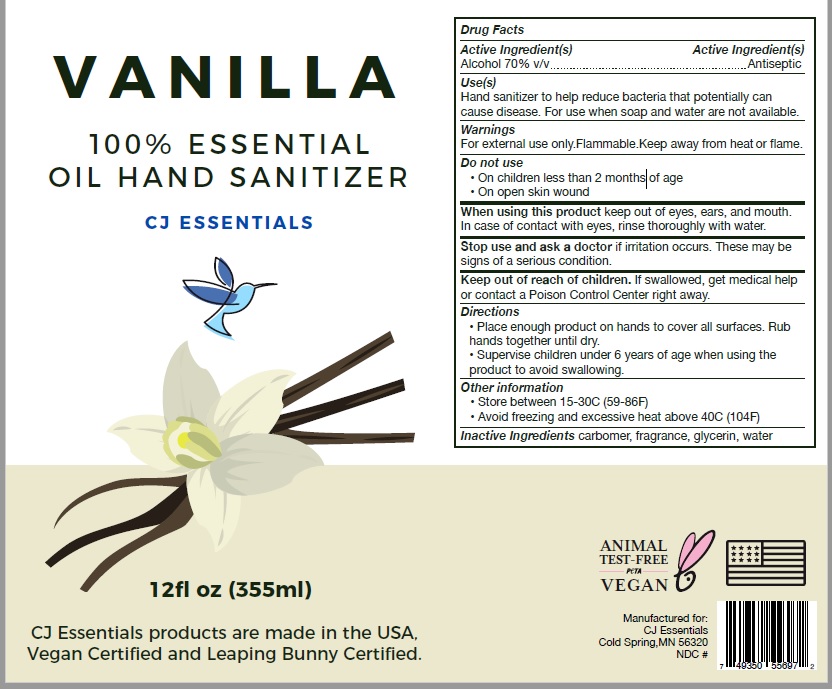 DRUG LABEL: CJ Essentials Vanilla hand sanitizer
NDC: 82320-002 | Form: LIQUID
Manufacturer: CJ Essentials
Category: otc | Type: HUMAN OTC DRUG LABEL
Date: 20211013

ACTIVE INGREDIENTS: ALCOHOL 70 mL/100 mL
INACTIVE INGREDIENTS: CARBOMER HOMOPOLYMER, UNSPECIFIED TYPE; GLYCERIN; WATER

Active Ingredient

Alcohol 70% v/v

Purpose

Antiseptic

Uses

Use hand sanitizer to help reduce bacteria that potentially can cause disease.
For use when soap and water are not available.

Warnings

For external use only. Flammable. Keep away from heat or flame.

Do not use

• On children less than 2 months of age
• On open skin wound

When using this product keep out of eyes, ears, and mouth.
In case of contact with eyes, rinse thoroughly with water

Stop use and ask a doctor if irritation occurs. These may be
signs of a serious condition.

Keep out of reach of children

If swallowed, get medical help or contact a Poison Control Center right away.

Directions

- Place enough product on hands to cover all surfaces. Rub hands together until dry.

• Supervise children under 6 years of age when using the product to avoid swallowing.

Other information

*Store between 15-30C (59-86F)
*Avoid freezing and excessive heat about 40C (104F)

Inactive Ingredients

carbomer, fragrance, glycerin, water